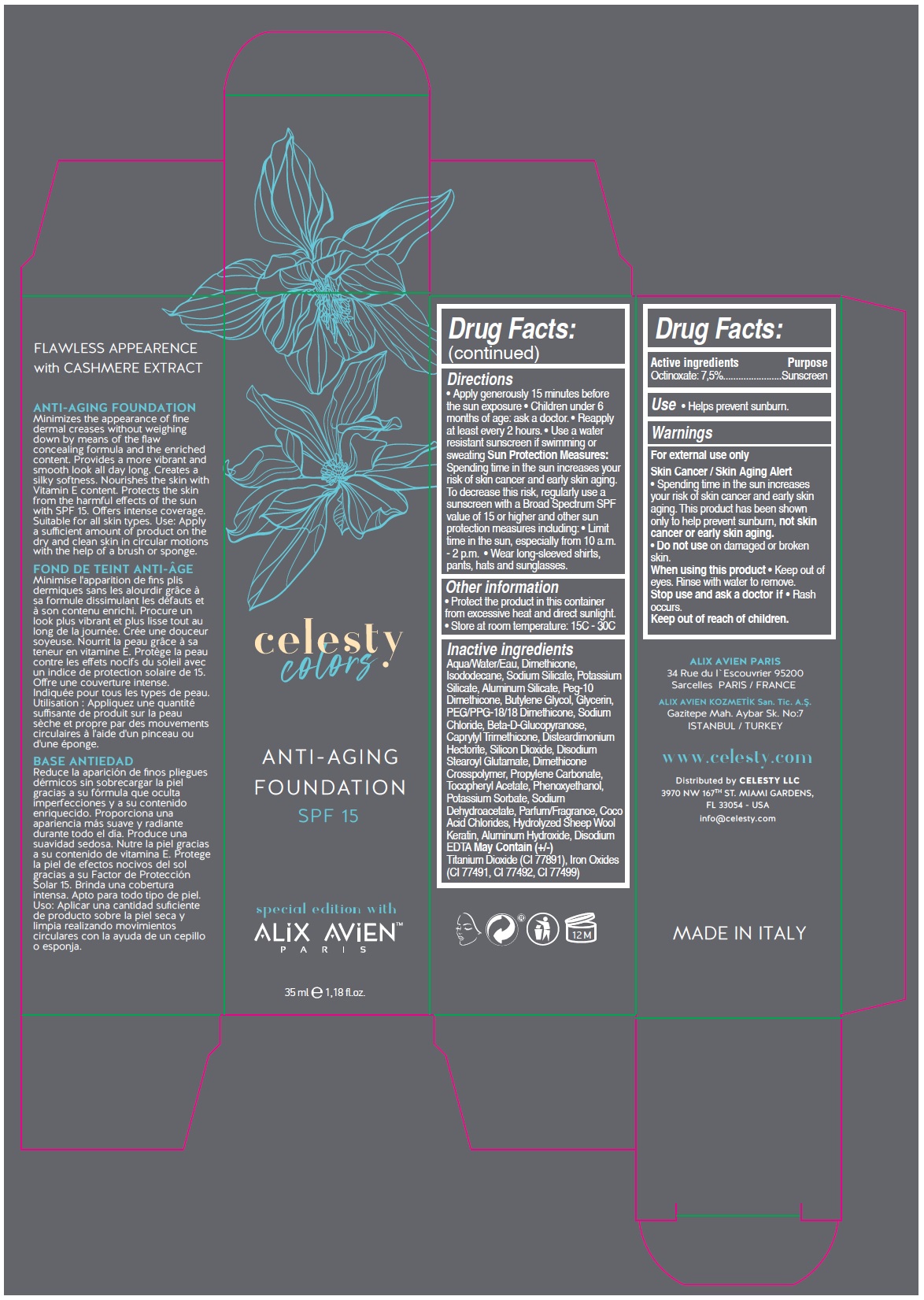 DRUG LABEL: celesty colors special edition with ALIX AVIEN
NDC: 81120-114 | Form: LOTION
Manufacturer: MABA KOZMETIK LIMITED SIRKETI
Category: otc | Type: HUMAN OTC DRUG LABEL
Date: 20210319

ACTIVE INGREDIENTS: OCTINOXATE 75 mg/1 mL
INACTIVE INGREDIENTS: WATER; DIMETHICONE; ISODODECANE; SODIUM SILICATE; POTASSIUM SILICATE; ALUMINUM SILICATE; PEG-10 DIMETHICONE (600 CST); BUTYLENE GLYCOL; GLYCERIN; PEG/PPG-18/18 DIMETHICONE; SODIUM CHLORIDE; .BETA.-D-GLUCOPYRANOSE; CAPRYLYL TRIMETHICONE; DISTEARDIMONIUM HECTORITE; SILICON DIOXIDE; DISODIUM STEAROYL GLUTAMATE; DIMETHICONE CROSSPOLYMER (450000 MPA.S AT 12% IN CYCLOPENTASILOXANE); PROPYLENE CARBONATE; .ALPHA.-TOCOPHEROL ACETATE; PHENOXYETHANOL; POTASSIUM SORBATE; SODIUM DEHYDROACETATE; COCO ACID CHLORIDES; HYDROLYZED SHEEP WOOL KERATIN (200 MW); ALUMINUM HYDROXIDE; EDETATE DISODIUM ANHYDROUS; TITANIUM DIOXIDE; FERRIC OXIDE RED; FERRIC OXIDE YELLOW; FERROSOFERRIC OXIDE

celesty colors special edition with ALIX AVIENTM ANTI-AGING FOUNDATION SPF 15

Active ingredients

Octinoxate: 7.5%

Purpose

Sunscreen

Use

• Helps prevent sunburn.

Warnings

For external use only

Skin Cancer / Skin Aging Alert
• Spending time in the sun increases your risk of skin cancer and early skin aging. This product has been shown only to help prevent sunburn, not skin cancer or early skin aging.

• Do not use on damaged or broken skin.

When using this product • Keep out of eyes. Rinse with water to remove.

Stop use and ask a doctor if • Rash occurs.

Keep out of reach of children.

Directions

• Apply generously 15 minutes before the sun exposure • Children under 6 months of age: ask a doctor. • Reapply at least every 2 hours. • Use a water resistant sunscreen if swimming or sweating Sun Protection Measures: Spending time in the sun increases your risk of skin cancer and early skin aging. To decrease this risk, regularly use a sunscreen with a Broad Spectrum SPF value of 15 or higher and other sun protection measures including: • Limit time in the sun, especially from 10 a.m. - 2 p.m. • Wear long-sleeved shirts, pants, hats and sunglasses.

Other information

• Protect the product in this container from excessive heat and direct sunlight.

• Store at room temperature: 15C - 30C

Inactive ingredients

Aqua/Water/Eau, Dimethicone, Isododecane, Sodium Silicate, Potassium Silicate, Aluminum Silicate, Peg-10 Dimethicone, Butylene Glycol, Glycerin, PEG/PPG-18/18 Dimethicone, Sodium Chloride, Beta-D-Glucopyranose, Caprylyl Trimethicone, Disteardimonium Hectorite, Silicon Dioxide, Disodium Stearoyl Glutamate, Dimethicone Crosspolymer, Propylene Carbonate, Tocopheryl Acetate, Phenoxyethanol, Potassium Sorbate, Sodium Dehydroacetate, Parfum/Fragrance, Coco Acid Chlorides, Hydrolyzed Sheep Wool Keratin, Aluminum Hydroxide, Disodium EDTA May Contain (+/-) Titanium Dioxide (CI 77891), Iron Oxides (CI 77491, CI 77492, CI 77499)

SPF 15

FLAWLESS APPEARANCE with CASHMERE EXTRACT

ANTI-AGING FOUNDATION
Minimizes the appearance of fine dermal creases without weighing down by means of the flaw concealing formula and the enriched content. Provides a more vibrant and smooth look all day long. Creates a silky softness. Nourishes the skin with the Vitamin E content. Protects the skin from the harmful effects of the sun with SPF 15. Offers intense coverage. Suitable for all skin types. Use: Apply a sufficient amount of product on the dry and clean skin in a circular motions with the help of a brush or sponge.

ALIX AVIEN PARIS

34 Rue du l'Escouvrier 95200
Sarcelles PARIS / FRANCE

ALIX AVIEN KOZMETİK San. Tic. A.Ş.

Gazitepe Mah. Aybar Sk. No:7
ISTANBUL / TURKEY

www.celesty.com

Distributed by CELESTY LLC
3970 NW 167TH ST. MIAMI GARDENS,
FL 33054 - USA
info@celesty.com

MADE IN ITALY